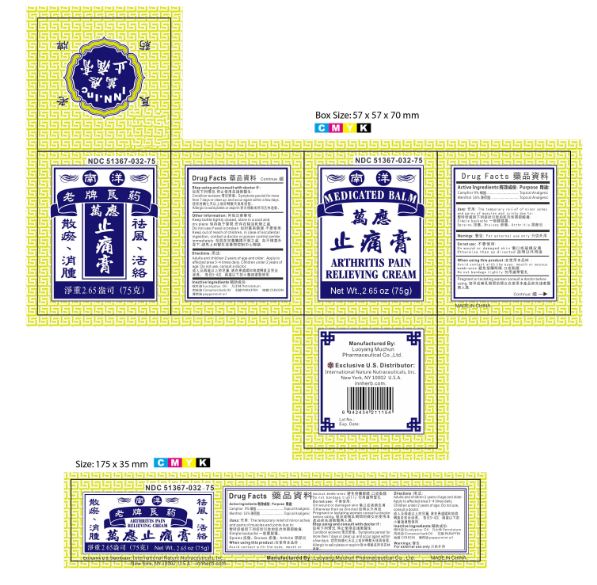 DRUG LABEL: Medicated Balm Arthritis Pain Relieving Cream
NDC: 51367-032 | Form: CREAM
Manufacturer: International Nature Nutraceuticals Inc.
Category: otc | Type: HUMAN OTC DRUG LABEL
Date: 20170926

ACTIVE INGREDIENTS: CAMPHOR (NATURAL) 6.75 g/1 1; MENTHOL 12 g/1 1
INACTIVE INGREDIENTS: EUCALYPTUS OIL; PETROLATUM; CINNAMON BARK OIL; PARAFFIN; CERESIN; PEPPERMINT OIL

Drug Facts

Active Ingredients

Camphor 9%

Menthol 16%

Uses

The temporary relief of minor aches and pains of muscles and joints due to:

Simple backache

Sprains

Bruises

Arthritis

Warnings

For External use only

Do not use:

On wound or damaged skin

Otherwise than as directed

Stop using and consult with doctor if:

Condition worsens

symptoms persist for more than 7 days or clear up and occur again within a few days

allergic to salicylates or aspirin

Other Information

Keep bottle tightly closed, store in a cool and dry place

Do not use if seal is broken

Directions

Adults and children 2 years of age and older: Apply to affected area 3-4 times daily

Children under 2 years of age: Do not use, consult a doctor

Keep out of reach of children

In case of accidental ingestion, contact a doctor or poision control center immediately

Inactive Ingreidents

Eucalyptus oil

Petrolatum

Cinnamon bark oil

Paraffin

Ceresin

Peppermint oil

Pregnant or lactating women

Consult a doctor before using

When using this product

Avoid contact with the eyes, mouth, or mucous membranes

Do not bandage tightly